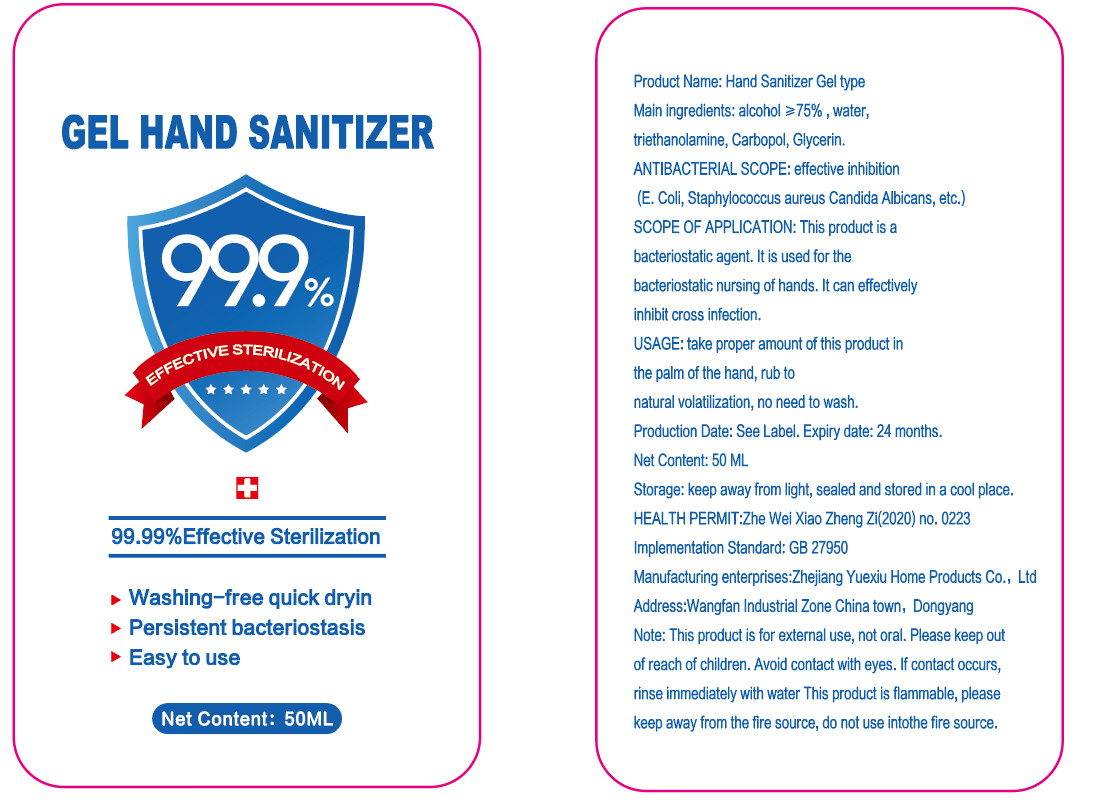 DRUG LABEL: Hand sanitizer
NDC: 78216-001 | Form: GEL
Manufacturer: Zhejiang Yuexiu Household Products Co., Ltd.
Category: otc | Type: HUMAN OTC DRUG LABEL
Date: 20200610

ACTIVE INGREDIENTS: ALCOHOL 37.5 mL/50 mL
INACTIVE INGREDIENTS: WATER; GLYCERIN; CARBOMER HOMOPOLYMER, UNSPECIFIED TYPE; TROLAMINE

DOSAGE AND ADMINISTRATION

keep away from light, sealed and stored in a cool place.

INACTIVE INGREDIENT

WATER、TRIETHANOLAMINE、CARBOPOL、Glycerol

INDICATIONS AND USAGE

take proper amount of this product in the palm of the hand, rub to natural vlilization, no need to wash.

ACTIVE INGREDIENT

ALCOHOL

keep out of reach of children

PURPOSE

Disinfection
Sterilization
No Rinseing

WARNINGS

This product is for extermal use, not oral. Please keep out of reach of children. Avoid contact with eyes. If contact occurs,rinse immediately with water This product is flammable, please keep away from the fire source, do not use intothe fire source.